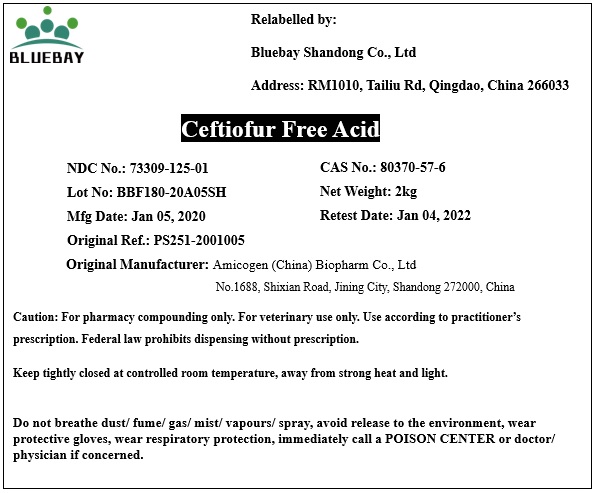 DRUG LABEL: Ceftiofur Free Acid
NDC: 73309-125 | Form: POWDER
Manufacturer: BLUEBAY SHANDONG CO.,LTD
Category: other | Type: BULK INGREDIENT
Date: 20200417

ACTIVE INGREDIENTS: CEFTIOFUR 1 kg/1 kg

Ceftiofur Free Acid